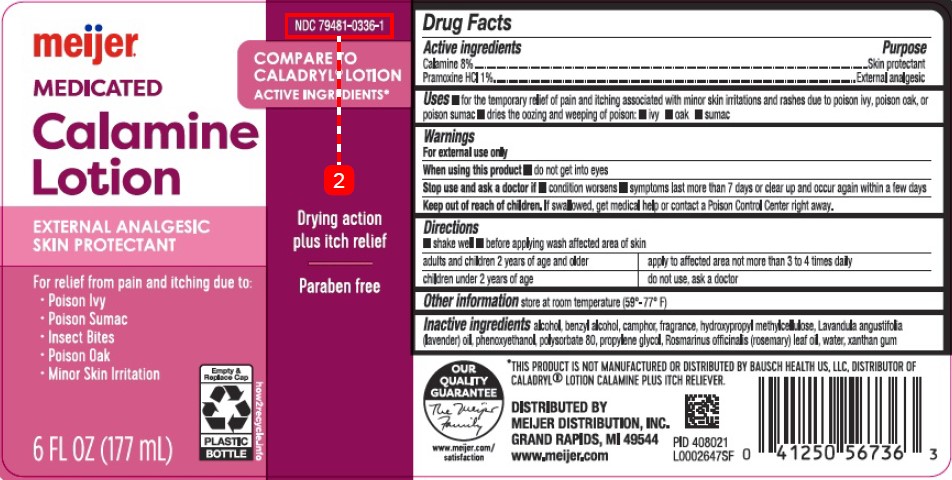 DRUG LABEL: Calamine
NDC: 79481-0336 | Form: LOTION
Manufacturer: Meijer, Inc.
Category: otc | Type: HUMAN OTC DRUG LABEL
Date: 20260219

ACTIVE INGREDIENTS: FERRIC OXIDE RED 80 mg/1 mL; PRAMOXINE HYDROCHLORIDE 10 mg/1 mL
INACTIVE INGREDIENTS: ALCOHOL; BENZYL ALCOHOL; CAMPHOR (SYNTHETIC); HYPROMELLOSE, UNSPECIFIED; LAVENDER OIL; PHENOXYETHANOL; POLYSORBATE 80; PROPYLENE GLYCOL; ROSEMARY OIL; WATER; XANTHAN GUM

Meijer 336.003/336AG
Medicated Calamine Lotion

Active ingredients

Calamine 8%

Pramoxine HCl 1%

Purpose

Skin protectant

External analgesic

Uses

- for the temporary relief of pain and itching associated with minot skin irritations and rashes due to poison ivy, poison oak, or poison sumac
- dries the oozing and weeping of poison:
- ivy
- oak
- sumac

Warnings

For external use only

When using this product

- do not get into eyes

Stop use and ask a doctor

- condition worsens
- symptoms last more than 7 days or clean up and occur again within a few days

Keep out of reach of children.

If swallowed, get medical help or contact a Poison Control Center right away.

Directions

- shake well
- before applying was affected are of skin

Adults and children 2 years of age and older - apply to affected area not more than 3 to 4 times daily

Children under 2 years of age - do not use, ask a doctor

Other information

store at room temperature (59°-77°F)

Inactive ingredients

alcohol, benzyl alcohol, camphor, fragrance, hydroxypropyl methylcellulose, Lavandula angustifolia (lavender) oil, phenoxyethanol, polysorbate 80, propylene glycol, Rosmarinus officinalis (rosemary) leaf oil, water, xanthan gum

Disclaimer

*THIS PRODUCT IS NOT MANUFACTURED OR DISTRIBUTED BY BAUSCH HEALTH US, LLC, DISTRIBUTOR OF CALADRYLLOTION CALAMINE PLUS ITCH RELIEVER.

Adverse Reaction

OUR QUALITY GUARANTEE

The Meijer Family

www.meijer.com/satisfaction

DISTRIBUTED BY MEIJER DISTRIBUTION, INC.

GRAND RAPIDS, MI 49544

www.meijer.com

Principal Panel Display

NDC 79481-0336-1

Compare to Caladryl®Lotion Active Ingredients*

meijer®

MEDICATED

Calamine

Lotion

External Analgesic

Skin Protectant

For relief from pain and itching due to:

- Poison Ivy
- Poison Sumac
- Insect Bites
- Poison Oak
- Minor Skin Irration

Empty & Replace Cap

Plastic Bottle

how2recycle.info

6 FL OZ (177 mL)